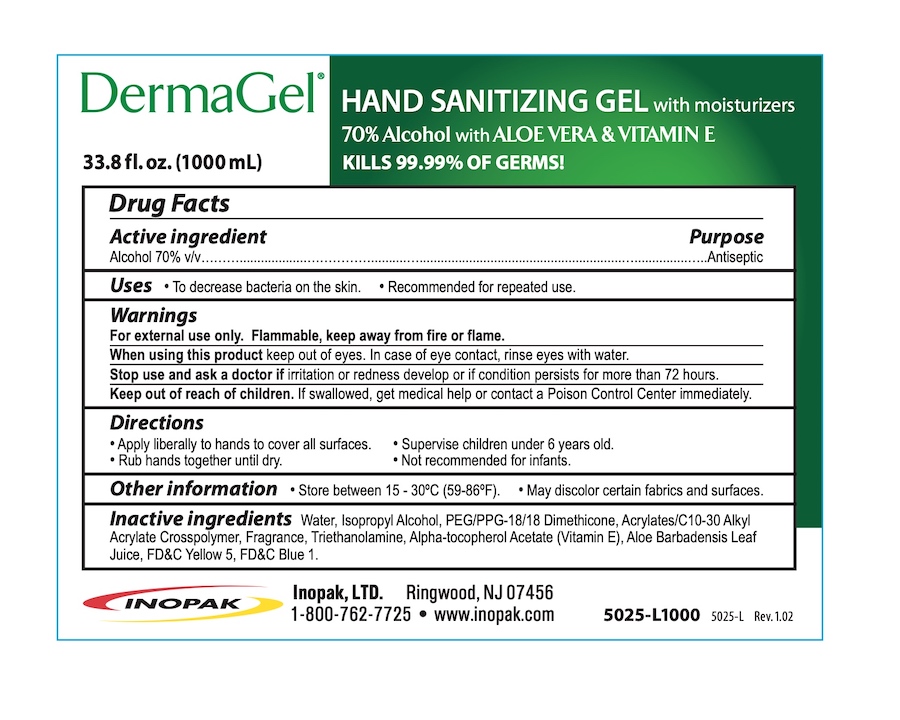 DRUG LABEL: DermaGel
NDC: 58575-130 | Form: GEL
Manufacturer: Inopak. Ltd
Category: otc | Type: HUMAN OTC DRUG LABEL
Date: 20210503

ACTIVE INGREDIENTS: ALCOHOL 70 mL/100 mL
INACTIVE INGREDIENTS: CARBOMER INTERPOLYMER TYPE B (ALLYL PENTAERYTHRITOL CROSSLINKED); ALPHA-TOCOPHEROL ACETATE; FD&C BLUE NO. 1; ALOE VERA LEAF; TROLAMINE; PEG/PPG-18/18 DIMETHICONE; FD&C YELLOW NO. 5; WATER; ISOPROPYL ALCOHOL

DermaGel Hand Sanitizing Gel

Drug Facts

Active ingredient

Alcohol 70% v/v

Purpose

Antiseptic

Uses

- To decrease bacteria on the skin.
- Recommended for repeated use.

Warnings

For external use only.

Flammable, keep away from fire or flame.

When using this product keep out of eyes. In case of eye contact, rinse eyes with water.

Stop use and ask a doctor if irritation and redness develop or if condition persists more than 72 hours.

Keep out of reach of children. If swallowed, get medical help or contact a Poison Control Center right away.

Directions

- Apply liberally to hands to cover all surfaces
- Rub hands together until dry.
- Supervise children under 6 years old.
- Not recommended for infants.

Other information

- Store between 15 - 30°C (59-86°F)
- May discolor certain fabrics and surfaces.

INACTIVE INGREDIENT

Inactive ingredients Water, Isopropyl Alcohol, PEG/PPG-18/18 Dimethicone, Acrylates / C10-30 Alkyl Acrylate Crosspolymer, Fragrance, Triethanolamine, Alpha-tocopheryl Acetate (Vitamin E), Aloe Barbadensis Leaf Juice, FD&C Yellow 5, FD&C Blue 1.

Inopak LTD.

Ringwood, NJ 07456

1-800-762-7725 • www.inopak.com

PACKAGE LABEL

DermaGel®

HAND SANITIZING GEL with moisturizers

70% Alcohol with ALOE VERA & VITAMIN E

33.8 fl. oz. (1000 mL)